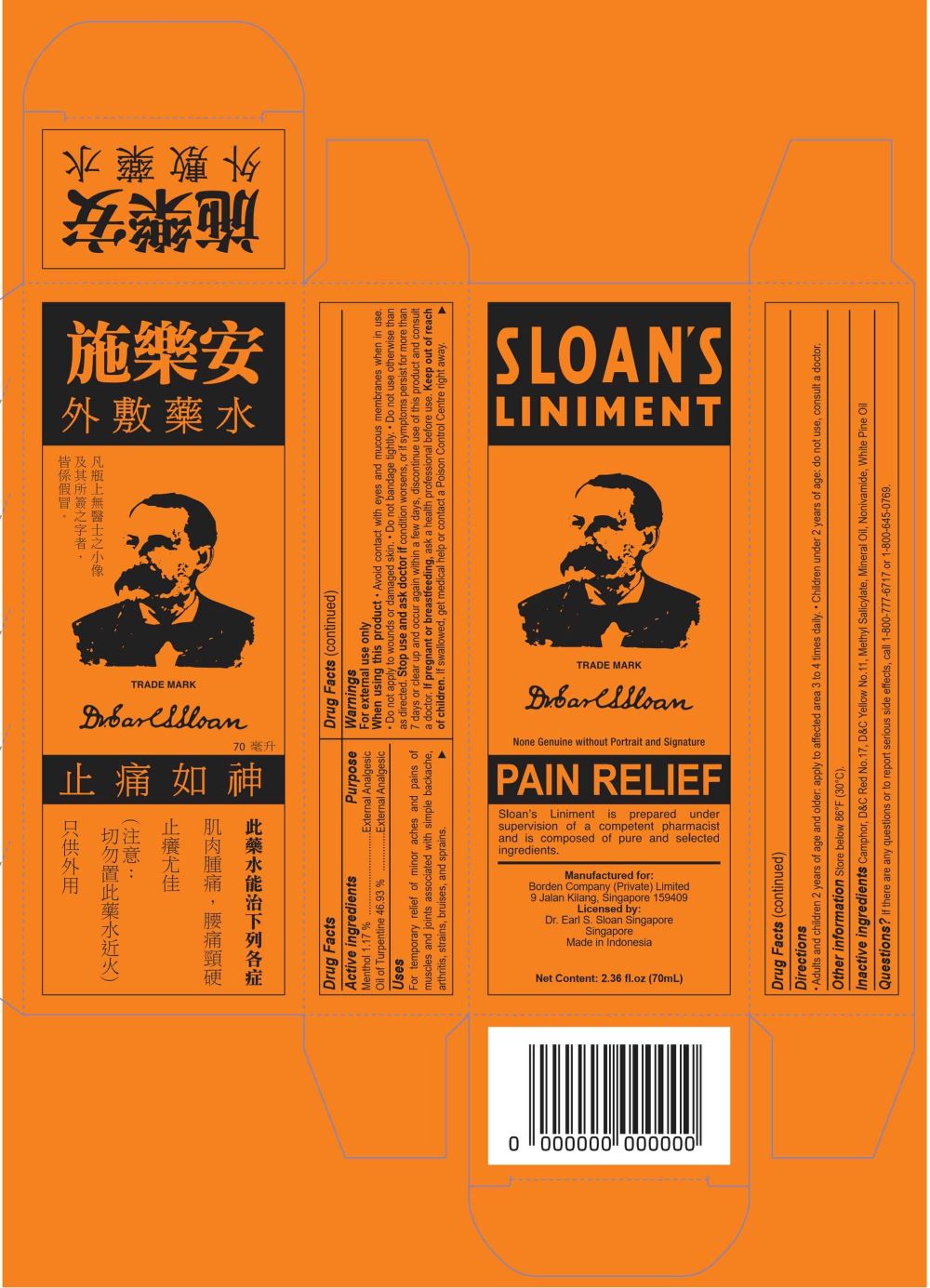 DRUG LABEL: SLOANS
NDC: 60954-009 | Form: LINIMENT
Manufacturer: PT. EAGLE INDO PHARMA
Category: otc | Type: HUMAN OTC DRUG LABEL
Date: 20250102

ACTIVE INGREDIENTS: MENTHOL 1.17 g/100 mL; TURPENTINE OIL 46.935 g/100 mL
INACTIVE INGREDIENTS: CAMPHOR (SYNTHETIC); D&C YELLOW NO. 11; MINERAL OIL; WHITE PINE OIL; D&C RED NO. 17; NONIVAMIDE; METHYL SALICYLATE

SLOAN'S LINIMENT

Active ingredients

- Menthol 1.17%
- Oil of Turpentine 46.935%

Purpose

External Analgesic

Uses

For temporary relief of minor aches and pains of muscles and joints associated with simple backache, arthritis, strains, bruises, and sprains

Warnings

For external use only

When using this product

- Avoid contact with eyes and mucous membranes when in use.
- Do not apply to wounds and damaged skin.
- Do not bandage tightly.
- Do not use otherwise than as directed.

Stop use and ask doctor if

Condition worsens, or if symptoms persist for more than 7 days or clear up and occur again, discontinue use of this product and consult a doctor.

If pregnant or breastfeeding

Ask a health professional before use.

Keep out of reach of children

If swallowed, get medical help or contact for Poison Control Centre right away.

Directions

- Adults and children 2 years of age and older: apply to affected area not more than 3 to 4 times daily.
- Children under 2 years of age: do not use, consult a doctor.

Other information

Store below 86oF (30oC).

Inactive ingredients

Camphor, D&C Red No.17, D&C Yellow No.11, Methyl Salicylate, Mineral Oil, Nonivamide, White Pine Oil

Questions?

If there are any questions or to report serious side effects, call 1-800-777-6717 or 1-800-645-0769.

Package Label

70ml NDC: 60954-009-70